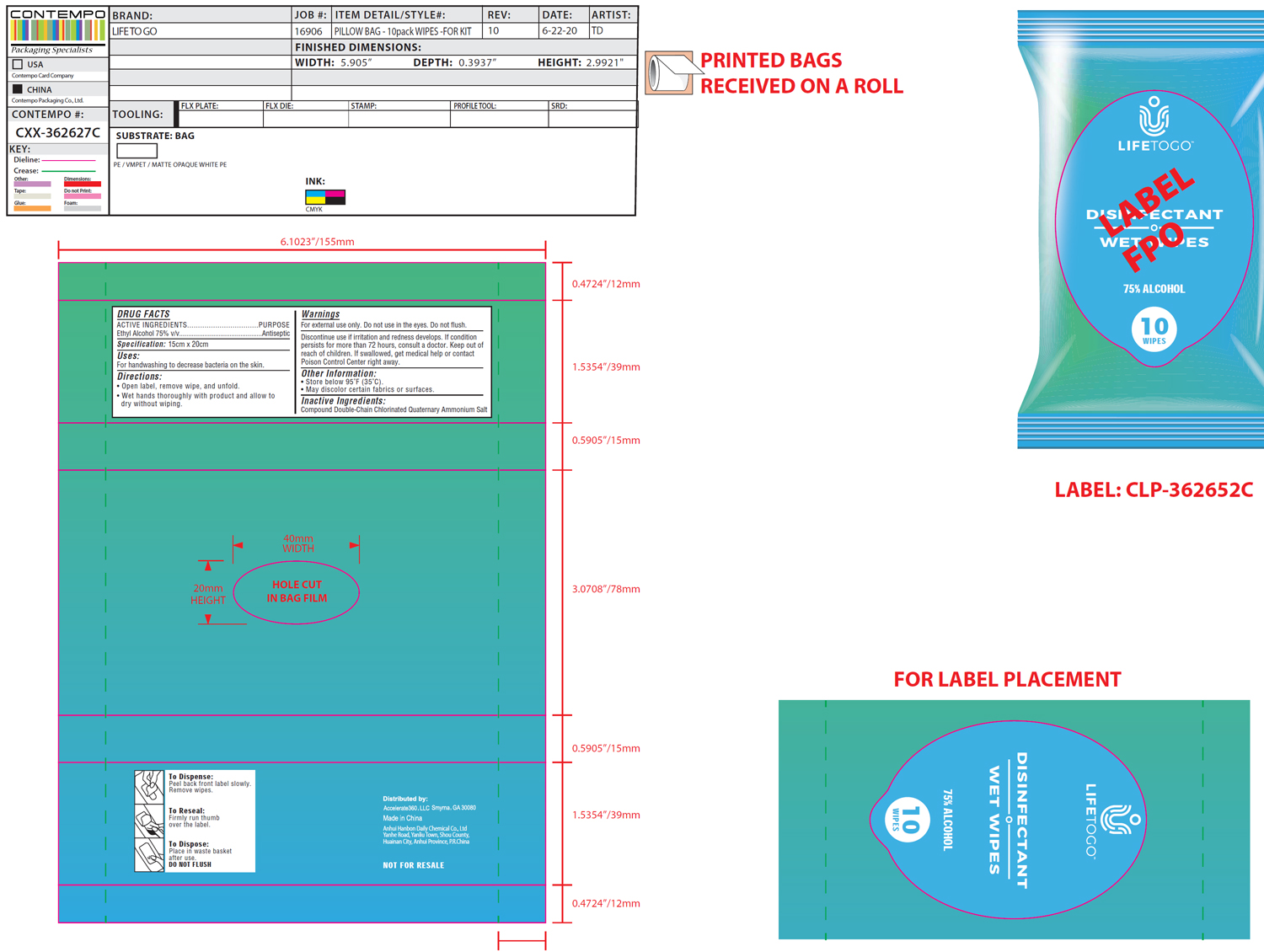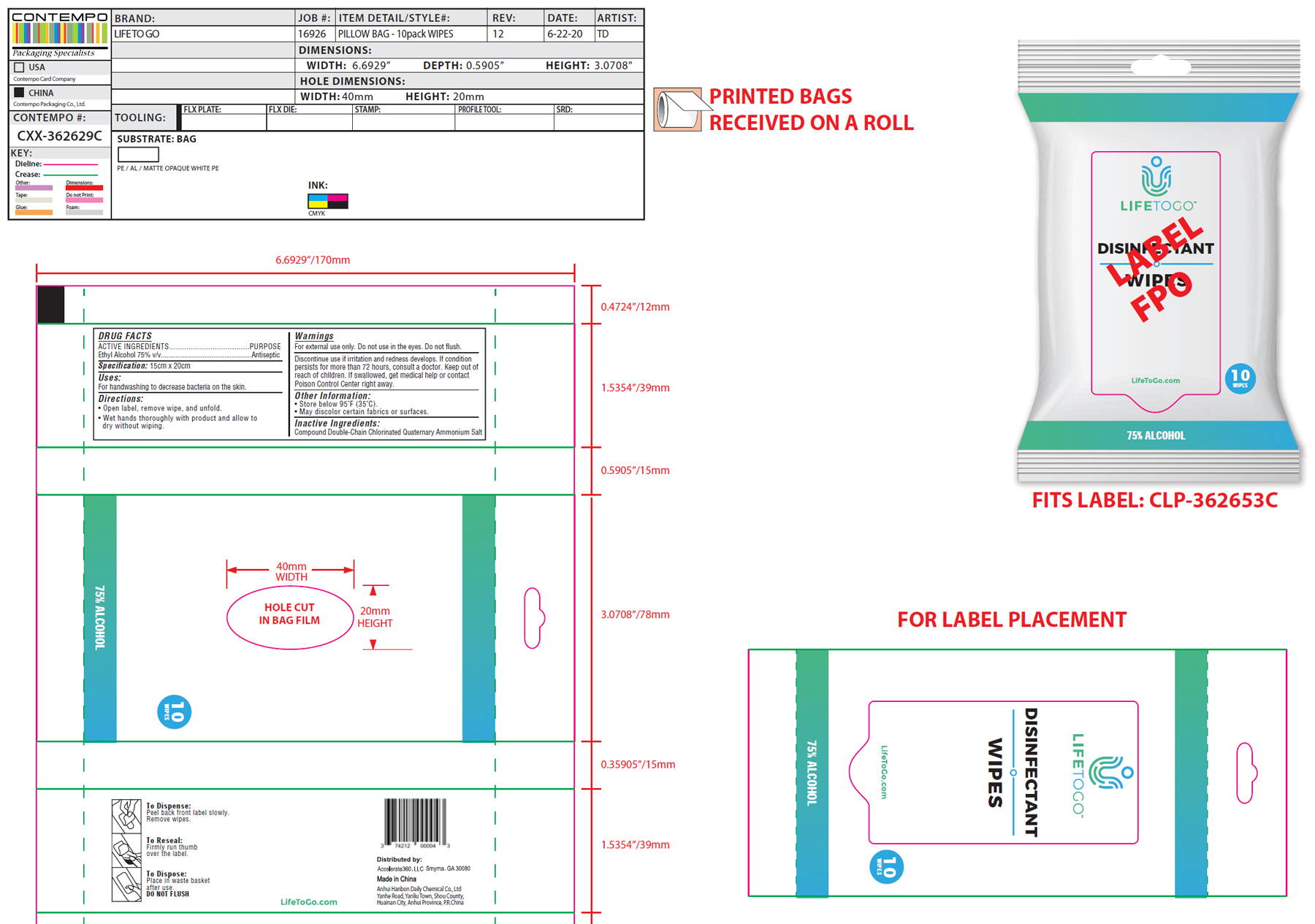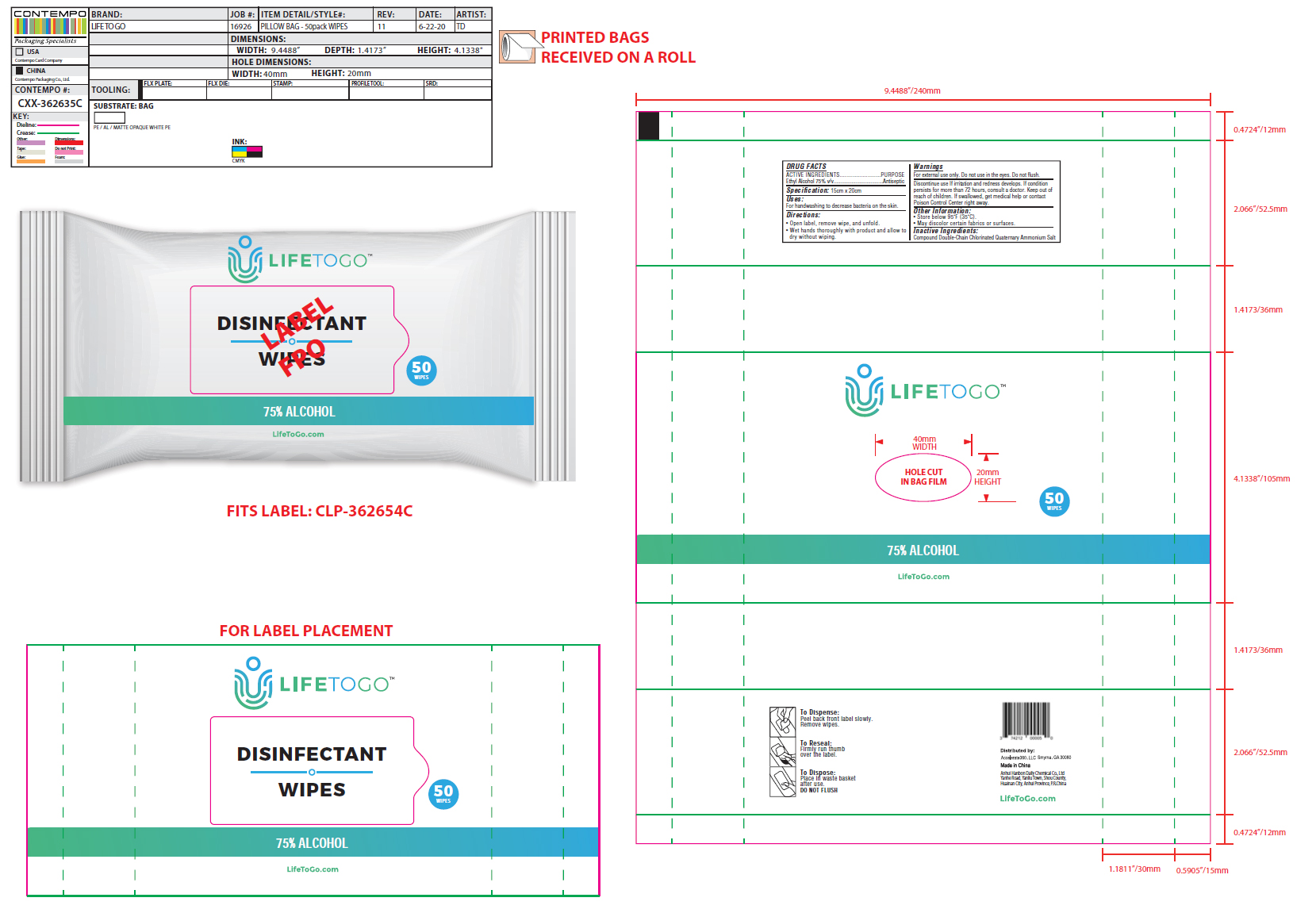 DRUG LABEL: DISINFECTANT WIPES
NDC: 74212-1002 | Form: CLOTH
Manufacturer: Accelerate360 Llc
Category: otc | Type: HUMAN OTC DRUG LABEL
Date: 20200811

ACTIVE INGREDIENTS: ALCOHOL 75 mL/100 g
INACTIVE INGREDIENTS: GLYCERIN; WATER; PROPYLENE GLYCOL; DIDECYLDIMONIUM CHLORIDE; BENZALKONIUM CHLORIDE; CETYLPYRIDINIUM CHLORIDE; N-ALKYL ETHYLBENZYL DIMETHYL AMMONIUM CHLORIDE (C12-C14)

DISINFECTANT WIPES

Active Ingredients

Ethyl Alcohol 75% v/v..............................................Antiseptic

Purpose

Antiseptic, wipes

Specification

15cm x 20cm

Uses

For handwashing to decrease bacteria on the skin.

Directions

- Open label, remove wipe, and unfold
- Wet hands thoroughly with product and allow to dry without wiping

Warnings

For external use only. Do not use in the eyes. Do not flush.

STOP USE

Discontinue use if irritation and redness develops. If condition persists for more than 72 hours, consult a doctor.

Keep out of reach of children. If swallowed, get medical help or contact a Poison Control Center right away.

Other information

- Store below 95F (35C)
- May discolor certain fabrics or surfaces

Inactive ingredients

Compound Double-Chain Chlorinated Quaternary Ammonium Salt

Package Label - Principal Display Panel

10PC NDC: 74212-1002-1

LIFETOGO

DISINFECTANT

WET WIPES

75% ALCOHOL

10 WIPES

10PC NDC: 74212-1002-2

LIFETOGO

DISINFECTANT

WIPES

LifeToGo.com

10 WIPES

75% ALCOHOL

50PC NDC: 74212-1002-3

LIFETOGO

DISINFECTANT

WIPES

50 WIPES

75% ALCOHOL

LifeToGo.com